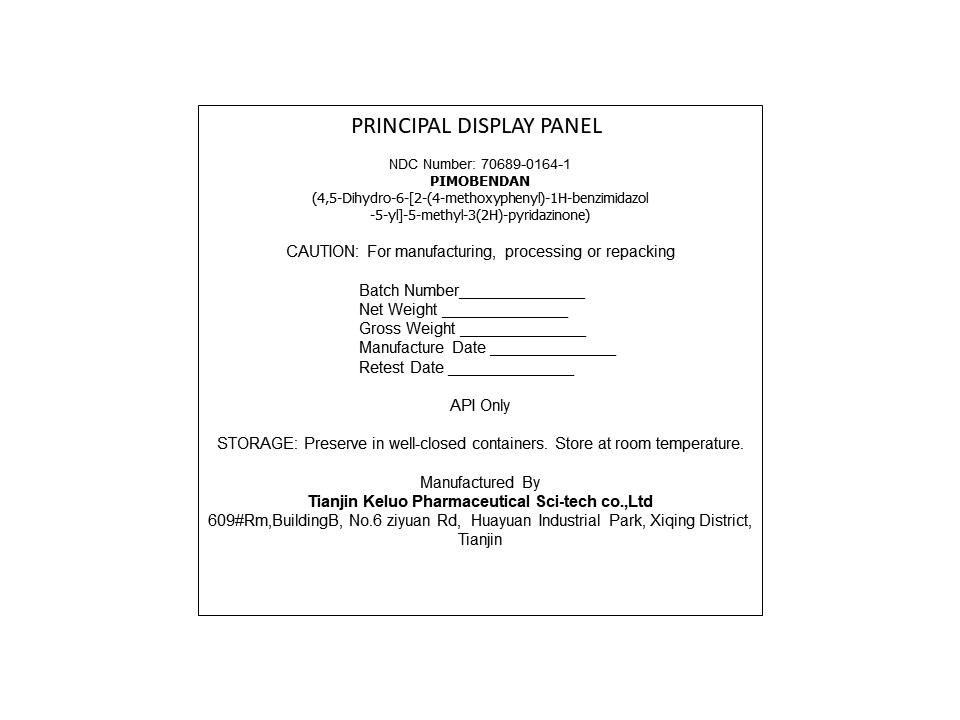 DRUG LABEL: Pimobendan
NDC: 70689-0164 | Form: POWDER
Manufacturer: Tianjin Kilo Pharmaceutical Scitech Co Ltd
Category: other | Type: BULK INGREDIENT - ANIMAL DRUG
Date: 20251217

ACTIVE INGREDIENTS: PIMOBENDAN 1 kg/1 kg

PACKAGE LABEL

PRINCIPAL DISPLAY PANEL

NDC Number: 70689-0164-1

PIMOBENDAN

(4,5-Dihydro-6-[2-(4-methoxyphenyl)-1H-benzimidazol

-5-yl]-5-methyl-3(2H)-pyridazinone)

CAUTION: For manufacturing, processing or repacking

Batch Number__________

Net Weight __________

Gross Weight__________

ManufactureDate__________

Retest Date___________

API Only

STORAGE: Preserve in well-closed containers. Store at room temperature.

Manufactured By

Tianjin Keluo Pharmaceutical Sci-tech co.,Ltd

609#Rm,BuildingB, No.6 ziyuan Rd, Huayuan Industrial Park, Xiqing District, Tianji